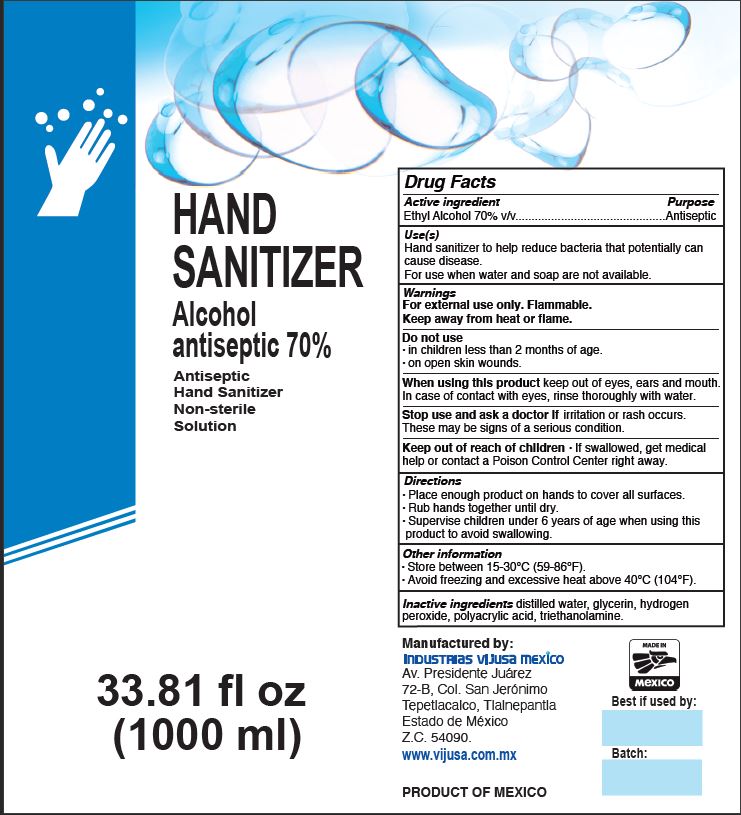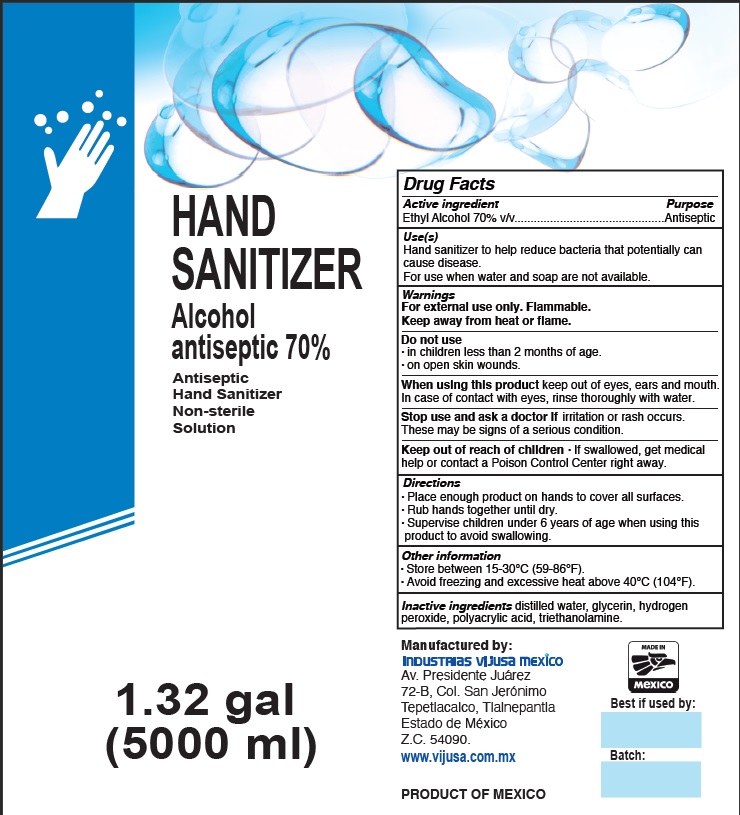 DRUG LABEL: Hand Sanitizer
NDC: 80711-002 | Form: GEL
Manufacturer: IVM Especialidades Quimicas, S.A. de C.V.
Category: otc | Type: HUMAN OTC DRUG LABEL
Date: 20250102

ACTIVE INGREDIENTS: ALCOHOL 70 mL/100 mL
INACTIVE INGREDIENTS: GLYCERIN; HYDROGEN PEROXIDE; WATER; CARBOMER INTERPOLYMER TYPE A (ALLYL SUCROSE CROSSLINKED); TROLAMINE

Hand Sanitizer Alcohol 80%

Active Ingredient(s)

Ethyl Alcohol 70% v/v. Purpose: Antiseptic

Purpose

Antiseptic.

Use

Hand Sanitizer to help reduce bacteria tt potentially can cause disease. For use when water and soap are not available.

Warnings

For external use only. Flammable.

Keep away from heat or flame.

Do not use

- in children less than 2 months of age
- on open skin wounds

When using this product

Keep out of eyes, ears, and mouth. In case of contact with eyes, rinse eyes thoroughly with water.

Stop use and ask a doctor if

irritation or rash occurs. These may be signs of a serious condition.

Keep out of reach of children.

If swallowed, get medical help or contact a Poison Control Center right away.

Directions

- Place enough product on hands to cover all surfaces. Rub hands together until dry.
- Supervise children under 6 years of age when using this product to avoid swallowing.

Other information

- Store between 15-30°C (59-86 °F)
- Avoid freezing and excessive heat above 40°C (104°F)

Inactive ingredients

distilled water, glycerin, hydrogen peroxide, polyacrylic acid, triethanolamine.

Package Label - Principal Display Panel

1000 mL NDC: 80711-002-01

PACKAGE LABEL

5000 ml NDC:80711-002-02